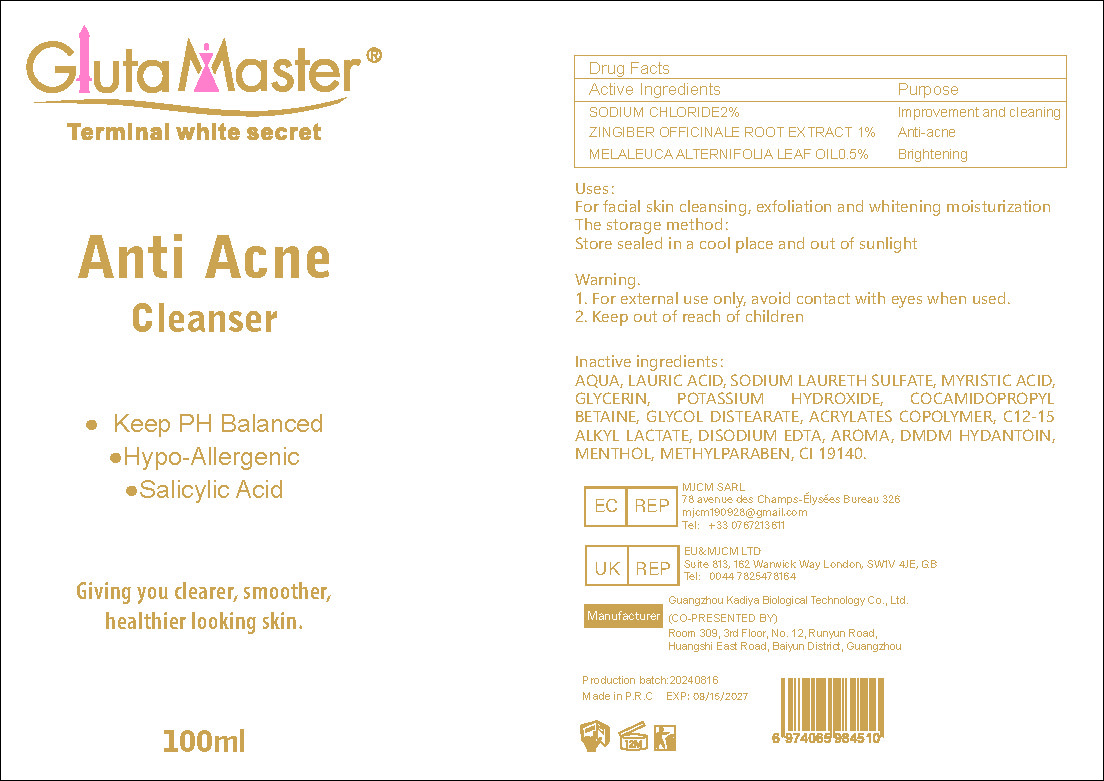 DRUG LABEL: Anti Acne Cleanser
NDC: 84423-038 | Form: CREAM
Manufacturer: Guangzhou Kadiya Biotechnology Co., Ltd.
Category: otc | Type: HUMAN OTC DRUG LABEL
Date: 20240826

ACTIVE INGREDIENTS: GINGER 1 mg/100 mL; MELALEUCA ALTERNIFOLIA (TEA TREE) LEAF OIL 0.5 mg/100 mL
INACTIVE INGREDIENTS: C12-15 ALKYL LACTATE; SODIUM LAURETH SULFATE; EDETATE DISODIUM; WATER; SODIUM CHLORIDE; GLYCERIN; MENTHOL; FD&C YELLOW NO. 5; DMDM HYDANTOIN; GLYCOL DISTEARATE; POTASSIUM HYDROXIDE; LAURIC ACID; MYRISTIC ACID; COCAMIDOPROPYL BETAINE; METHYLPARABEN

PURPOSE

For the improvement and lightening of redness on the face

INACTIVE INGREDIENT

AQUA、LAURIC ACID、SODIUM LAURETH SULFATE、MYRISTIC ACID、GLYCERIN
、POTASSIUM HYDROXIDE、COCAMIDOPROPYL BETAINE、GLYCOL DISTEARATE、ACRYLATES COPOLYMER、C12-15 ALKYL LACTATE、DISODIUM EDTA、AROMA、DMDM HYDANTOIN、MENTHOL、METHYLPARABEN、CI 19140

Warning.
1、For external use only, avoid contact with eyes when used
2、Keep out of reach of children

INDICATIONS AND USAGE

For facial skin cleansing, exfoliation and whitening moisturization

DOSAGE AND ADMINISTRATION

For facial skin cleansing, exfoliation and whitening moisturization

Active Ingredients
SODIUM CHLORIDE2%
ZINGIBER OFFICINALE ROOT EXTRACT 1%
MELALEUCA ALTERNIFOLIA LEAF OIL0.5%

KEEP OUT OF REACH OF CHILDREN SECTION

PACKAGE LABEL

Active Ingredients
SODIUM CHLORIDE2%
ZINGIBER OFFICINALE ROOT EXTRACT 1%
MELALEUCA ALTERNIFOLIA LEAF OIL0.5%

Uses：
For the improvement and lightening of redness on the face
The storage method：
Store sealed in a cool place and out of sunlight

Warning.
1、For external use only, avoid contact with eyes when used
2、Keep out of reach of children

Inactive ingredients：
AQUA、LAURIC ACID、SODIUM LAURETH SULFATE、MYRISTIC ACID、GLYCERIN
、POTASSIUM HYDROXIDE、COCAMIDOPROPYL BETAINE、GLYCOL DISTEARATE、ACRYLATES COPOLYMER、C12-15 ALKYL LACTATE、DISODIUM EDTA、AROMA、DMDM HYDANTOIN、MENTHOL、METHYLPARABEN、CI 19140